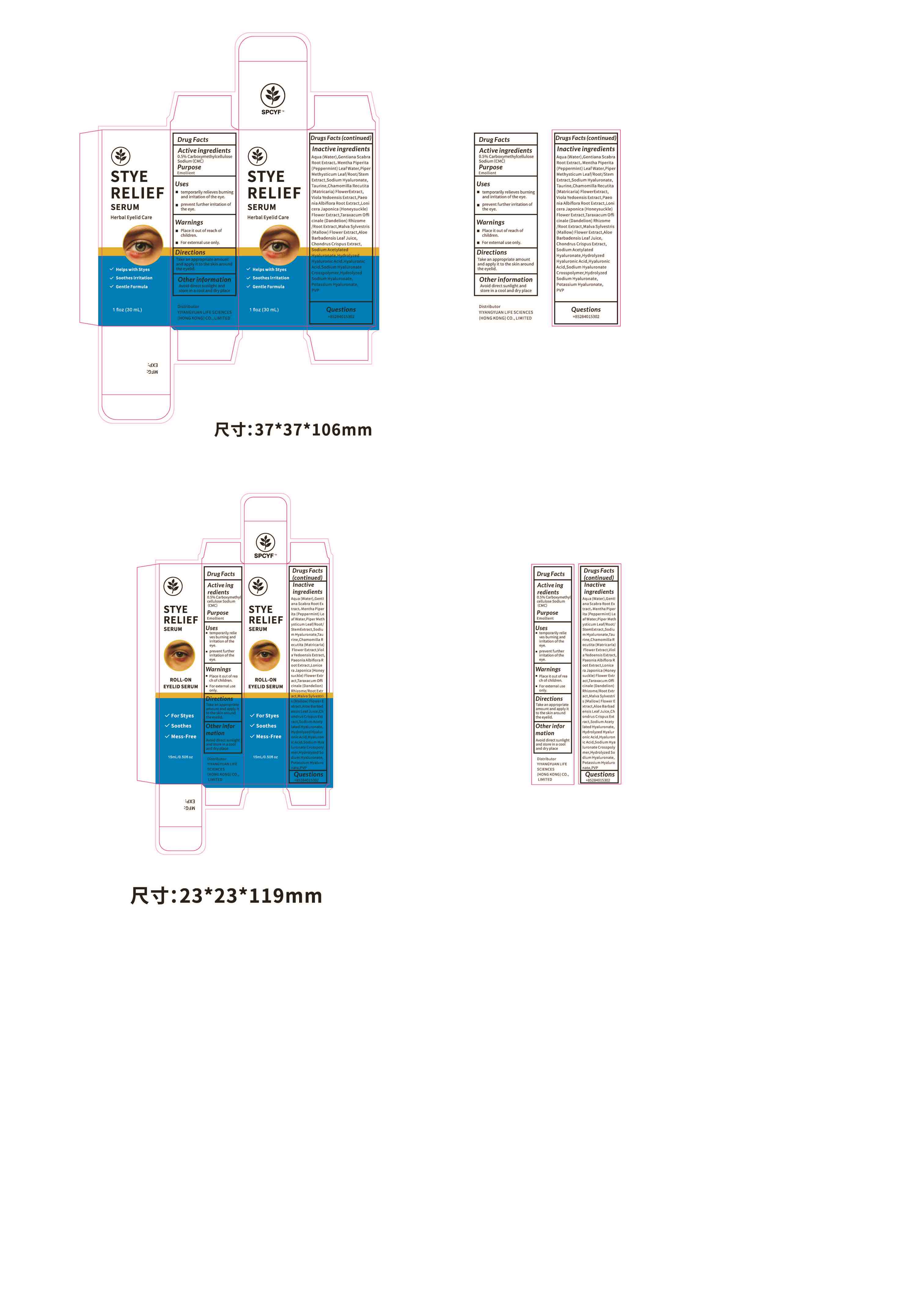 DRUG LABEL: STYE RELIEF SERUM
NDC: 87183-001 | Form: PASTE
Manufacturer: Guangzhou Shimei Cosmetics Co., Ltd.
Category: otc | Type: HUMAN OTC DRUG LABEL
Date: 20251215

ACTIVE INGREDIENTS: CARBOXYMETHYLCELLULOSE SODIUM 0.5 g/100 mL
INACTIVE INGREDIENTS: TARAXACUM OFFICINALE (DANDELION) ROOT; HYALURONIC ACID; GENTIANA SCABRA ROOT; HUMAN SKIN PROTEINS, PARTIALLY HYDROLYZED; CHONDRUS CRISPUS CARRAGEENAN; POTASSIUM HYPOPHOSPHITE; AQUA; MATRICARIA CHAMOMILLA WHOLE; LONICERA JAPONICA FLOWER; VIOLA PHILIPPICA WHOLE; SODIUM ACETYLATED HYALURONATE; PVP; PIPER METHYSTICUM ROOT; PAEONIA LACTIFLORA ROOT; MALVA SYLVESTRIS FLOWERING TOP; MENTHA PIPERITA (PEPPERMINT) LEAF; SODIUM HYALURONATE; TAURINE; ALOE BARBADENSIS LEAF POWDER

ACTIVE INGREDIENT

Active ingredients CarboxymethylcelluloseSodium(CMC) 0.5% Purpose Emollient

Keep out of reach of children

PURPOSE

Helps with styes

Soothes lrritation

Gentle Formula

WARNINGS

For external use only.

INDICATIONS AND USAGE

temporarily relieves burningand irritation of the eye.prevent further irritation ofthe eye.

Directions
Take an appropriate amountand apply it to the skin aroundthe eyelid.

Inactive ingredients
Aqua(Water),Gentiana ScabraRoot Extract,Mentha Piperita(Peppermint)LeafWater,PipeMethysticum Leaf/Root/StemExtract,Sodium Hyaluronate,Taurine,ChamomillaRecutita(Matricaria) FlowerExtract,Viola Yedoensis Extract,Paeonia Albiflora Root Extract,Lonicera Japonica (Honeysuckle)Flower Extract,Taraxacum Officinale(Dandelion)Rhizome/Root Extract,Malva Sylvestris(Mallow)Flower Extract,AloeBarbadensis Leaf Juice,
Chondrus Crispus Extract,
Sodium Acetylated
Hyaluronate,HydrolyzedHyaluronic Acid,HyaluronicAcid,Sodium HyaluronateCrosspolymer,HydrolyzedSodium Hyaluronate,Potassium Hyaluronate.PVP